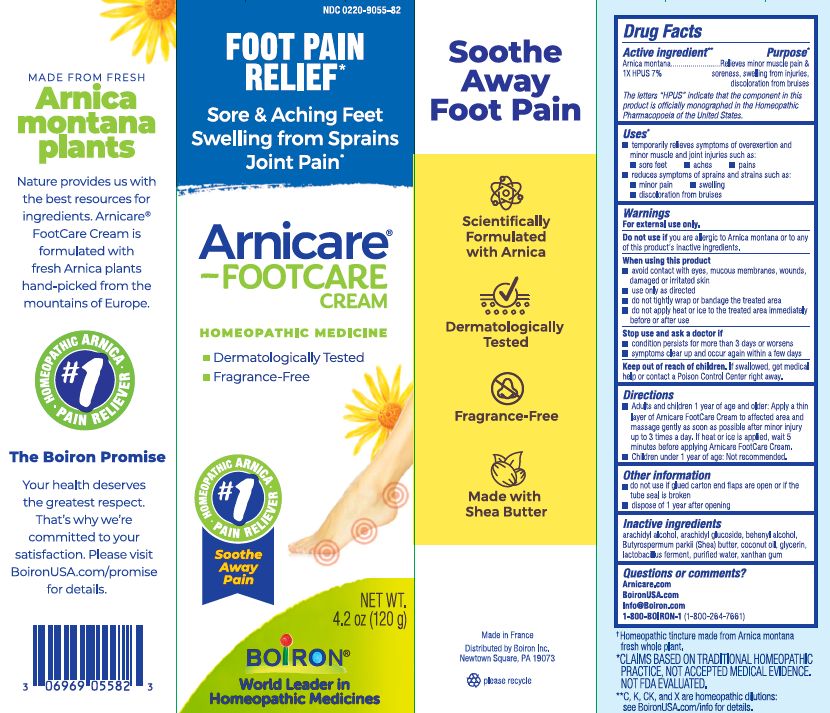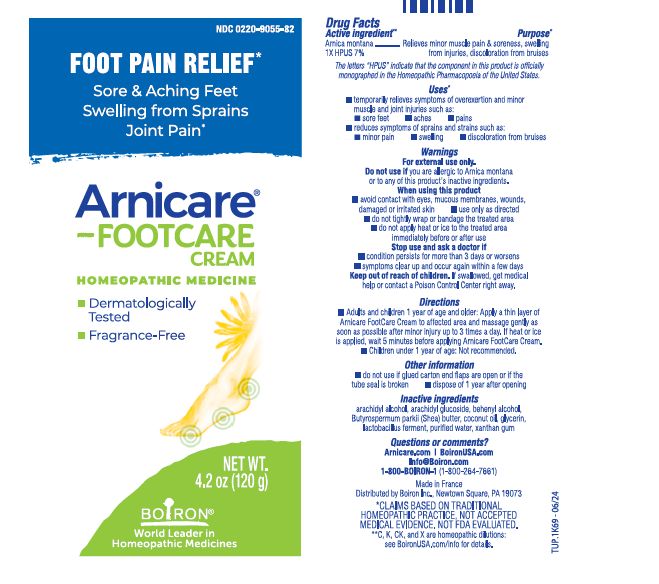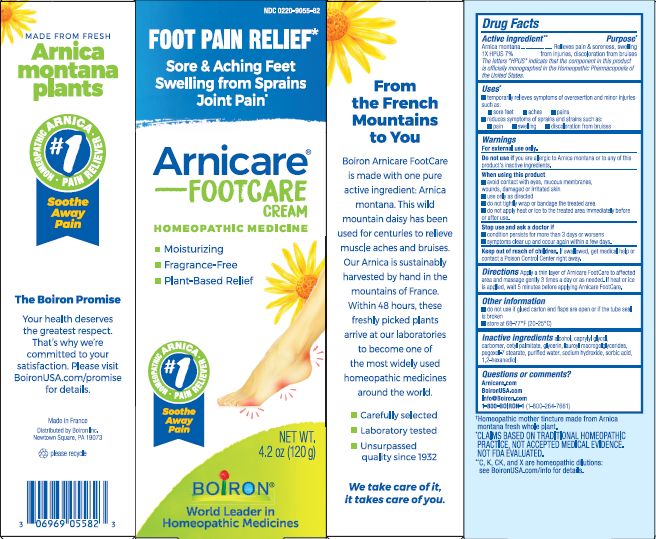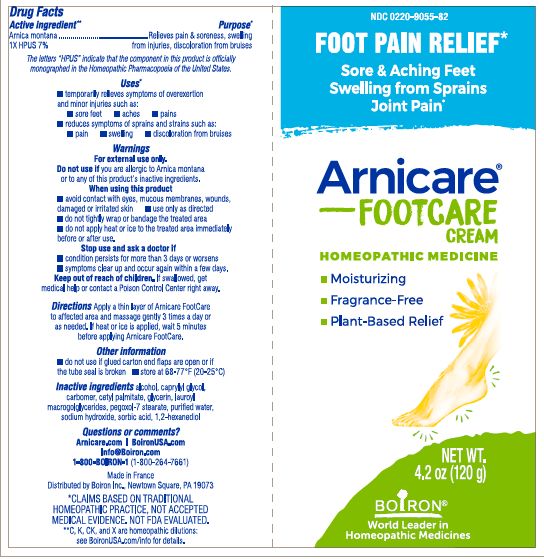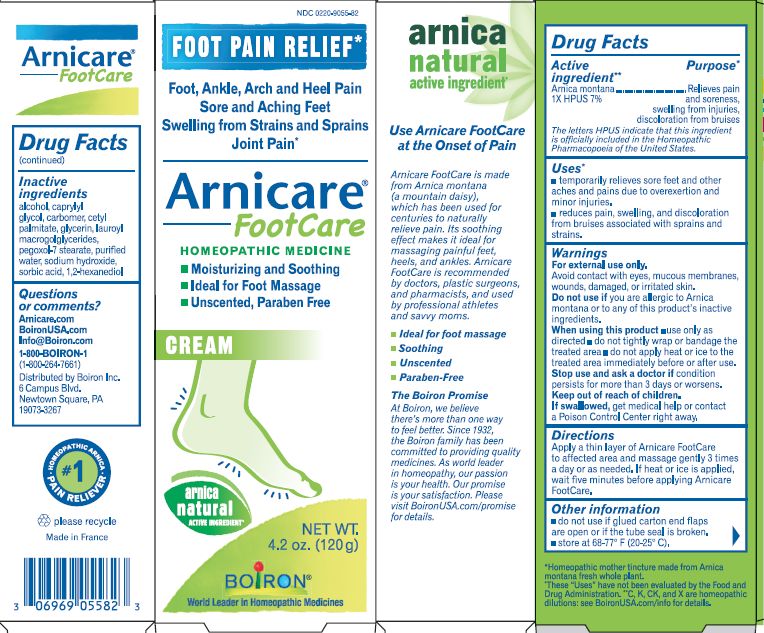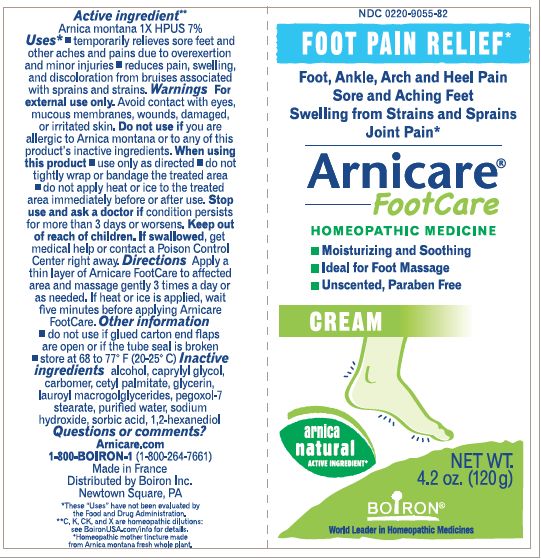 DRUG LABEL: Arnicare Foot Care
NDC: 0220-9055 | Form: CREAM
Manufacturer: Boiron
Category: homeopathic | Type: HUMAN OTC DRUG LABEL
Date: 20251114

ACTIVE INGREDIENTS: ARNICA MONTANA 1 [hp_X]/1 [hp_X]
INACTIVE INGREDIENTS: BUTYROSPERMUM PARKII (SHEA) BUTTER UNSAPONIFIABLES; LIMOSILACTOBACILLUS FERMENTUM; WATER; XANTHAN GUM; COCONUT OIL; GLYCERIN; ARACHIDYL ALCOHOL; DOCOSANOL; ARACHIDYL GLUCOSIDE

Arnicare Foot Care

Active Ingredient **

Arnica montana 1X HPUS 7%

The letters "HPUS" indicate that the components in this product are officially monographed in the Homeopathic Pharmacopoeia of the United States.

Purpose*

Relieves minor muscle pain & soreness, swelling from injuries, discoloration from bruises

Uses*

temporarily relieves symptoms of overexertion and minor muscle and joint injuries such as:

- sore feet
- aches
- pains
- reduces symptoms of sprains and strains such as:
- minor pain
- swelling
- discoloration from bruises

Warnings

For external use only.

Do not use if you are allergic to Arnica montana or to any of this product's inactive ingredients.

When using this product

- avoid contact with eyes, mucous membranes, wounds, damaged or irritated skin
- use only as directed
- do not tightly wrap or bandage the treated area
- do not apply heat or ice to the treated area immediately before or after use

Stop use and ask a doctor if

- condition persists for more than 3 days or worsen
- symptoms clear up and occur again within a few days

Keep out of reach of children. If swallowed, get medical help or contact Poison Control Center right away.

Directions

- Adults and children 1 year of age and older: Apply a thin layer of Arnicare FootCare Cream to affected area and massage gently as soon as possible after minor injury up to 3 times a day. If heat or ice is applied, wait 5 minutes before applying Arnicare FootCare Cream.
- Children under 1 year of age: Not recommended.

do not use if glued carton end flaps are open or if the tube seal is broken.

dispose of 1 year after opening

4.2 oz (120g)

Sore & Aching Feet Swelling from Sprains Joint Pain*

Foot Pain Relief*

ɨ Homeopathic mother tincture made from Arnica montana fresh whole plant.

*CLAIMS BASED ON TRADITIONAL HOMEOPATHIC PRACTICE, NOT ACCEPTED MEDICAL EVIDENCE. NOT FDA EVALUATED.
*C,K,CK, and X are homeopathic dilutions: see BoironUSA.com/info for details.

INACTIVE INGREDIENT

arachidyl alcohol, arachidyl glucoside, behenyl alcohol, Butyrospermum parkii (Shea) butter, coconut oil, glycerin, lactobacillus ferment, purified water, xanthan gum

QUESTIONS

Arnicare.com

BoironUSA.com

Info@Boiron.com

1-800-BOIRON-1

(1-800-264-7661)

Distributed by Boiron Inc.

Newtown Square, PA 19073-3267